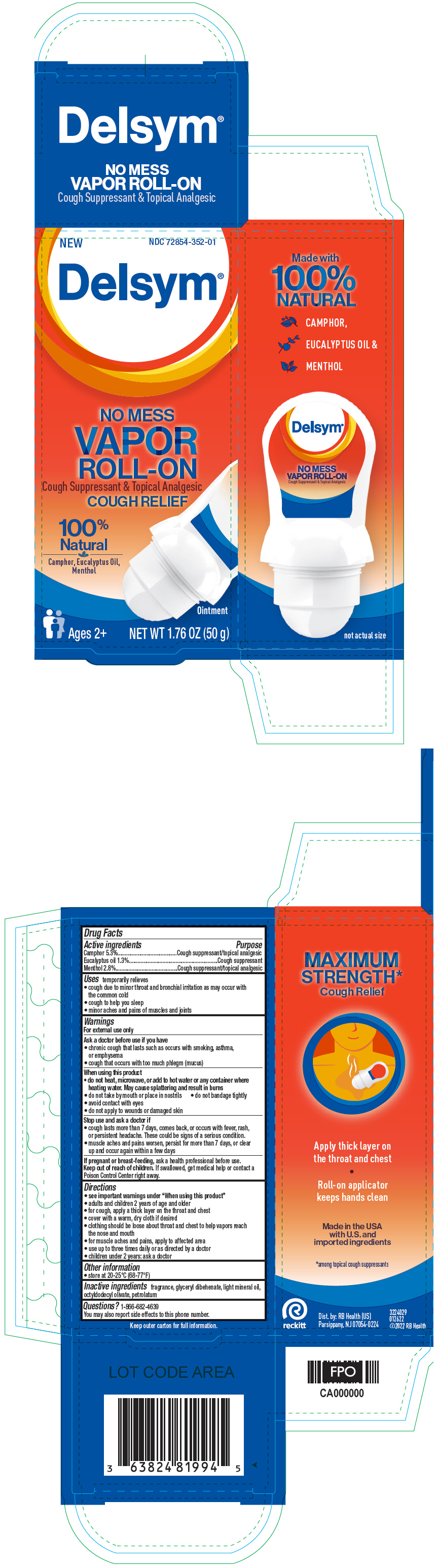 DRUG LABEL: DELSYM
NDC: 72854-352 | Form: OINTMENT
Manufacturer: RB Health (US) LLC
Category: otc | Type: HUMAN OTC DRUG LABEL
Date: 20241223

ACTIVE INGREDIENTS: CAMPHOR (NATURAL) 53 mg/1 g; EUCALYPTUS OIL 13 mg/1 g; MENTHOL, UNSPECIFIED FORM 28 mg/1 g
INACTIVE INGREDIENTS: GLYCERYL DIBEHENATE; LIGHT MINERAL OIL; PETROLATUM; OCTYLDODECYL OLEATE

DELSYM®
NO MESS VAPOR ROLL ON

Drug Facts

ACTIVE INGREDIENT

Active ingredients | Purpose
Camphor 5.3% | Cough suppressant/topical analgesic
Eucalyptus oil 1.3% | Cough suppressant
Menthol 2.8% | Cough suppressant/topical analgesic

Uses

temporarily relieves

- cough due to minor throat and bronchial irritation as may occur with the common cold
- cough to help you sleep
- minor aches and pains of muscles and joints

Warnings

For external use only

Ask a doctor before use if you have

- chronic cough that lasts such as occurs with smoking, asthma, or emphysema
- cough that occurs with too much phlegm (mucus)

When using this product

- do not heat, microwave, or add to hot water or any container where heating water. May cause splattering and result in burns
- do not take by mouth or place in nostrils
- do not bandage tightly
- avoid contact with eyes
- do not apply to wounds or damaged skin

Stop use and ask a doctor if

- cough lasts more than 7 days, comes back, or occurs with fever, rash, or persistent headache. These could be signs of a serious condition.
- muscle aches and pains worsen, persist for more than 7 days, or clear up and occur again within a few days

PREGNANCY OR BREAST FEEDING

If pregnant or breast-feeding,ask a health professional before use.

Keep out of reach of children.If swallowed, get medical help or contact a Poison Control Center right away.

Directions

- see important warnings under " When using this product"
- adults and children 2 years of age and older
- for cough, apply a thick layer on the throat and chest
- cover with a warm, dry cloth if desired
- clothing should be loose about throat and chest to help vapors reach the nose and mouth
- for muscle aches and pains, apply to affected area
- use up to three times daily or as directed by a doctor
- children under 2 years: ask a doctor

Other information

- store at 20-25°C (68-77°F)

Inactive ingredients

fragrance, glyceryl dibehenate, light mineral oil, octyldodecyl olivate, petrolatum

Questions?

1-866-682-4639

You may also report side effects to this phone number.

Dist. by: RB Health (US)
Parsippany, NJ 07054-0224

PRINCIPAL DISPLAY PANEL - 50 g Container Carton

NEW
NDC 72854-352-01

Delsym®

NO MESS
VAPOR
ROLL-ON
Cough Suppressant & Topical Analgesic
COUGH RELIEF

100%
Natural
Camphor, Eucalyptus Oil,
Menthol

Ointment

Ages 2+

NET WT 1.76 OZ (50 g)